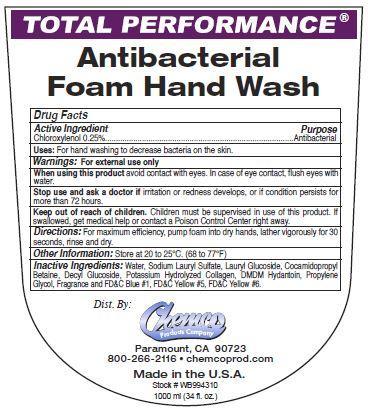 DRUG LABEL: Antibacterial Foam Hand Wash
NDC: 63039-1005 | Form: LIQUID
Manufacturer: Chemco Products Company
Category: otc | Type: HUMAN OTC DRUG LABEL
Date: 20241125

ACTIVE INGREDIENTS: CHLOROXYLENOL 2.5 mg/1 mL
INACTIVE INGREDIENTS: WATER; SODIUM LAURYL SULFATE; LAURYL GLUCOSIDE; COCAMIDOPROPYL BETAINE; DECYL GLUCOSIDE; DMDM HYDANTOIN; PROPYLENE GLYCOL; FD&C BLUE NO. 1; FD&C YELLOW NO. 5; FD&C YELLOW NO. 6

Drug Facts
63039-1005

Active Ingredient

Chloroxylenol 0.25%

Purpose

Antibacterial

Uses:

For hand washing to decrease bacteria on the skin.

Warnings:

For external use only

When using this product avoid contact with eyes.

In case of eye contact, flush eyes with water.

Stop use and ask a doctor if irritation or redness develops, or if condition persists for more than 72 hours.

Keep out of reach of children.

Children must be supervised in use of this product.

If swallowed, get medical help or contact a Poison Control Center right away.

Directions:

For maximum efficiency, pump foam into dry hands, lather vigorously for 30 seconds, rinse and dry.

Other Information:

Store at 20 to 25 C. (68 to 77 F)

Inactive Ingredients:

Water, Sodium Lauryl Sulfate, Lauryl Glucoside, Cocamidopropyl Betaine, Decyl Glucoside, Potassium Hydrolyzed Collagen, DMDM Hydantoin, Propylene Glycol, Fragrance, and FDC Blue #1, FDC Yellow #5, FDC Yellow #6.

PACKAGE LABEL

Total Performance

Antibacterial

Foam Hand Wash

Dist.By:

Chemco

Products Company

Paramount, CA 90723

800-266-2116 chemcoprod.com

Made in the U.S.A.

Stock # WB994310

1000 ml (34 fl. oz.)